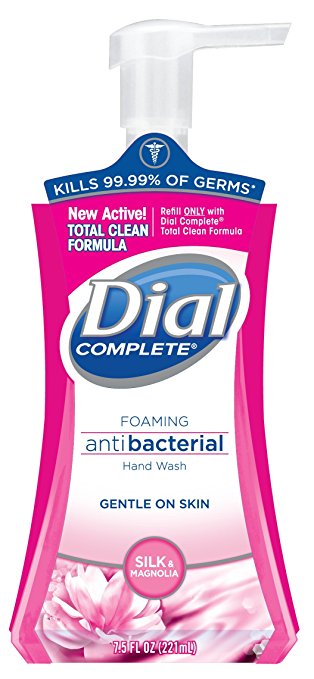 DRUG LABEL: DIAL FOAMING HAND WASH
NDC: 54340-261 | Form: LIQUID
Manufacturer: The Dial Corporation, A Henkel Company
Category: otc | Type: HUMAN OTC DRUG LABEL
Date: 20160101

ACTIVE INGREDIENTS: BENZETHONIUM CHLORIDE 0.2 g/100 mL
INACTIVE INGREDIENTS: WATER 93.8 g/100 mL

Dial Complete Silk & Magnolia Foaming Antibacterial Hand Wash

Dial Complete Healthier Skin, Healthier You

KILLS MORE GERMS

Than Ordinary Liquid Hand Soap

Others*

After washing with other ordinary hand soap.

Dial Complete*

After washing with Dial Complete Foaming Antibacterial Hand Wash

*Dramatization only: Number of organisms shown does not reflect actual number of bacteria.

Active Ingredient

Benzethonium Chloride 0.2%

PURPOSE

Antibacterial

USE

For handwashing to decrease bacteria on the skin.

For external use only.

When using this product

avoid contact with eyes. In case of eye contact, flush with water.

Stop use and ask a doctor if irritation or redness develops.

Keep out of reach of children.

If swallowed, get medical help or contact a Poison Control Center right away.

Directions

- Pump into DRY hands
- Lather vigorously for at least 15 seconds
- Rinse and dry thoroughly

Inactive Ingredients

Aqua (Water, Eau), Glycerin, Lauramine Oxide, Sunflowerseedamidopropyl Ethyldimonium Ethosulfate with PEG-9, Cocamidopropyl Betaine, Hydroxypropyl Methylcellulose, DMDM Hydantoin, Chlorohexidine Digluconate, Parfum (Fragrance), Citric Acid, Sodium Chloride, Zinc Sulfate, Dimethyl Lauramine,Tetrasodium EDTA, Hydrolyzed Silk, CI 17200 (Red 33)

Questions

1 800 258 DIAL

* Encountered in household settings

** Antibacterial Liquid Hand Wash

REFILL ONLY WITH DIAL COMPLETE ® TOTAL CLEAN FORMULA

©2015 & Distributed by THE DIAL CORPORATION

A Henkel Company
SCOTTSDALE, AZ 85255

Made in USA

The distinctive design and elements of this package are propriatary and
owned by The dial Corporation, A Henkel Company

Patent #6,107,261

PACKAGE LABEL

TOTAL CLEAN FORMULA

Refill ONLY with Dial Complete® Total Clean Formula

Dial Complete® Foaming antibacterial Hand Wash

Gentle on skin

SILK & MAGNOLIA

7.5 FL OZ (221 mL)